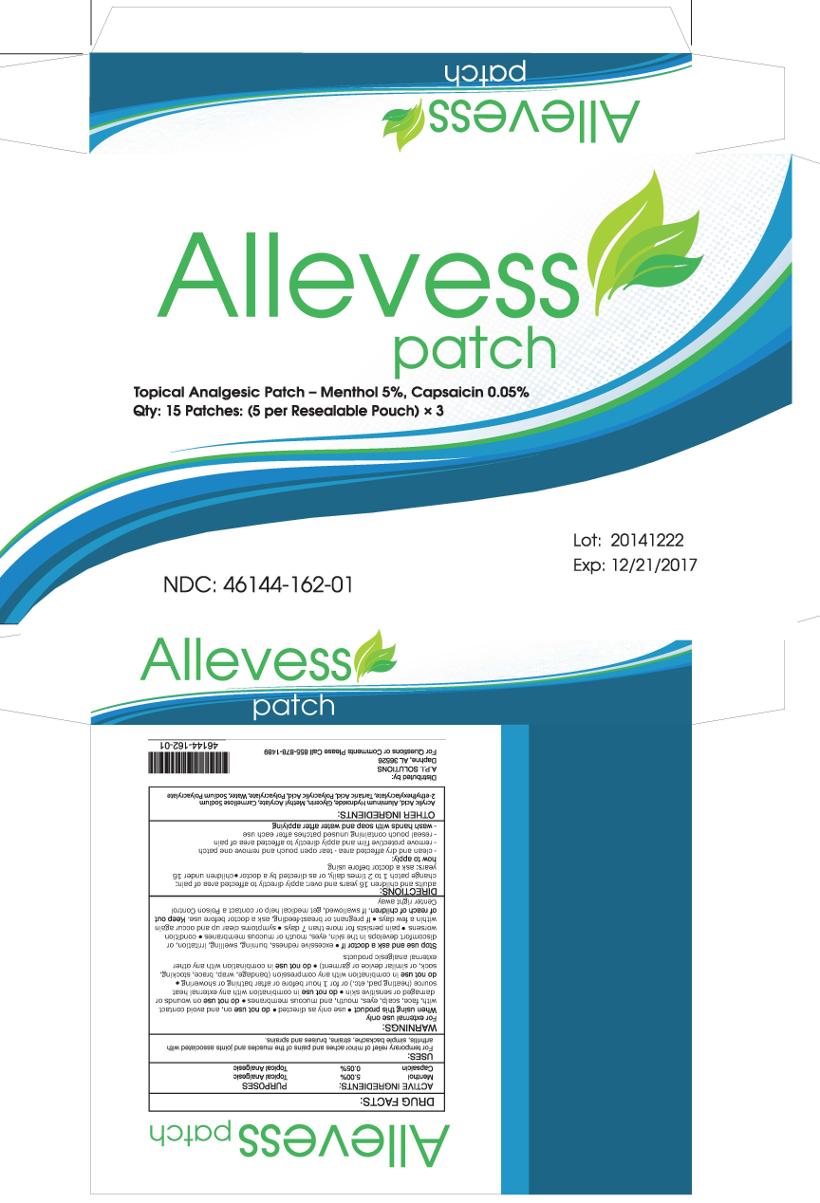 DRUG LABEL: ALLEVESS
NDC: 46144-162 | Form: PATCH
Manufacturer: API Solutions, Inc.
Category: otc | Type: HUMAN OTC DRUG LABEL
Date: 20151202

ACTIVE INGREDIENTS: MENTHOL 5 g/100 g; CAPSAICIN 0.05 g/100 g
INACTIVE INGREDIENTS: Acrylic Acid; Aluminum Hydroxide; Glycerin; Methyl Acrylate; CARBOXYMETHYLCELLULOSE SODIUM, UNSPECIFIED FORM; 2-Ethylhexyl Acrylate; Tartaric Acid; POLYACRYLIC ACID (8000 MW); Water; SODIUM POLYACRYLATE (2500000 MW)

API Solutions - Allevess Patch

ACTIVE INGREDIENTS:

MENTHOL 5.00%
CAPSAICIN 0.05%

PURPOSES:

TOPICAL ANALGESIC
TOPICAL ANALGESIC

USES:

FOR TEMPORARY RELIEF OF MINOR ACHES AND PAINS OF THE MUSCLES AND JOINTS ASSOCIATED WITH ARTHRITIS, SIMPLE BACKACHE, STRAINS, BRUISES AND SPRAINS.

WARNINGS:

FOR EXTERNAL USE ONLY.

WHEN USING THIS PRODUCT

∙ USE ONLY AS DIRECTED

DO NOT USE ON, AND AVOID CONTACT WITH, FACE, SCALP, EYES, MOUTH, AND MUCOUS MEMBRANES ∙ DO NOT USE ON WOUNDS OR DAMAGED OR SENSITIVE SKIN ∙ DO NOT USE IN COMBINATION WITH ANY EXTERNAL HEAT SOURCE (HEATING PAD, ETC.) OR FOR 1 HOUR BEFORE OR AFTER BATHING OR SHOWERING ∙ DO NOT USE IN COMBINATION WITH ANY COMPRESSION (BANDAGE, WRAP, BRACE, STOCKING, SOCK, OR SIMILAR DEVICE OR GARMENT) ∙ DO NOT USE IN COMBINATION WITH ANY OTHER EXTERNAL ANALGESIC PRODUCTS.

STOP USE AND ASK A DOCTOR IF ∙ EXCESSIVE REDNESS, BURNING, SWELLING, IRRITATION, OR DISCOMFORT DEVELOPS IN THE SKIN, EYES, MOUH OR MUCOUS MEMBRANES ∙ CONDITION WORSENS ∙ PAIN PERSISTS FOR MORE THAN 7 DAYS ∙ SYMPTOMS CLEAR UP AND OCCUR AGAIN WITHIN A FEW DAYS

IF PREGNANT OR BREAST-FEEDING,

ASK A DOCTOR BEFORE USE.

KEEP OUT OF REACH OF CHILDREN.

IF SWALLOWED, GET MEDICAL HELP OR CONTACT A POISON CONTROL CENTER RIGHT AWAY.

DIRECTIONS:

ADULTS AND CHILDREN 16 YEARS AND OVER: APPLY DIRECTLY TO AFFECTED AREA OF PAIN; CHANGE PATCH 1 TO 2 TIMES DAILY, OR AS DIRECTED BY A DOCTOR ∙ CHILDREN UNDER 16 YEARS: ASK A DOCTOR BEFORE USING

HOW TO APPLY:
− CLEAN AND DRY AFFECTED AREA - TEAR OPEN POUCH AND REMOVE ONE PATCH
− REMOVE PROTECTIVE FILM AND APPLY DIRECTLY TO AFFECTED AREA OF PAIN
− RESEAL POUCH CONTAINING UNUSED PATCHES AFTER EACH USE
− WASH HANDS WITH SOAP AND WATER AFTER APPLYING

OTHER INGREDIENTS:

ACRYLIC ACID, ALUMINUM HYDROXIDE, GLYCERIN, METHYL ACRYLATE, CARMELLOSE SODIUM, 2-ETHYLHEXYL ACRYLATE, TARTARIC ACID, POLYACRYLATE, POLYACRYLIC ACID, WATER, SODIUM POLYACRYLATE

QUESTIONS

DISTRIBUTED BY:
A.P.I. SOLUTIONS
DAPHNE, AL 36526
FOR QUESTIONS OR COMMENTS PLEASE CALL 855-878-1489

Principal Display Panel

ALLEVESS PATCH

TOPICAL ANALGESIC PATCH - MENTHOL 5%, CAPSAICIN 0.05%
QTY: 15 PATCHES: (5 PER RESEALABLE POUCH) × 3

LOT:
EXP:
NDC: 46144-162-01